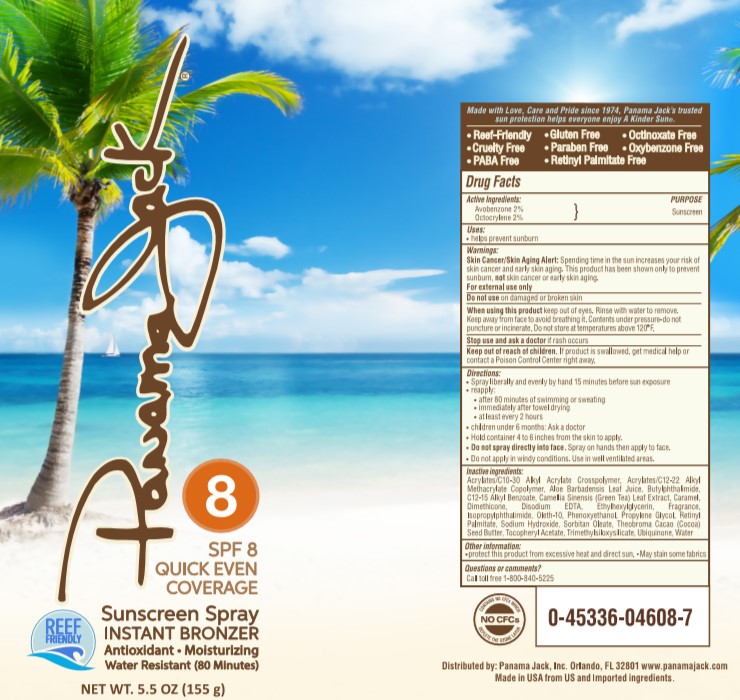 DRUG LABEL: Panama Jack
NDC: 13630-0174 | Form: SPRAY
Manufacturer: Prime Packaging, Inc.
Category: otc | Type: HUMAN OTC DRUG LABEL
Date: 20201001

ACTIVE INGREDIENTS: AVOBENZONE 2 g/100 g; OCTOCRYLENE 2 g/100 g
INACTIVE INGREDIENTS: ISOPROPYLPHTHALIMIDE; VITAMIN A PALMITATE; COCOA BUTTER; CARBOMER INTERPOLYMER TYPE A (ALLYL SUCROSE CROSSLINKED); ALOE VERA LEAF; TRIMETHYLSILOXYSILICATE (M/Q 0.8-1.0); ALKYL (C12-15) BENZOATE; WATER; BUTYL ACRYLATE/METHYL METHACRYLATE/METHACRYLIC ACID COPOLYMER (18000 MW); DIMETHICONE; ETHYLHEXYLGLYCERIN; EDETATE DISODIUM ANHYDROUS; PHENOXYETHANOL; N-BUTYLPHTHALIMIDE; GREEN TEA LEAF; CARAMEL; PROPYLENE GLYCOL; SODIUM HYDROXIDE; UBIDECARENONE; SORBITAN MONOOLEATE; .ALPHA.-TOCOPHEROL ACETATE; OLETH-10; FRAGRANCE LAVENDER & CHIA F-153480

Panama Jack SPF 8 Bronzer Lotion C/S

Active ingredients

Avobenzone 2 %, Octocrylene 2 %

Purpose

Sunscreen

Uses

- helps prevent sunburn

Warnings

Skin Cancer/Skin Aging Alert: Spending time in the sun increases your risk of skin cancer and early skin aging. This product has been shown only to prevent sunburn, not skin cancer or early skin aging.

OTHER SAFETY INFORMATION

For external use only

Do not use on damaged or broken skin.

When using this product keep out of eyes. Rinse with water to remove. Keep away from face to avoid breathing it. Contents under pressure - do not puncture or incinirate. Do not store at temperatures above 120^0F

Stop use and ask a doctor if rash occurs.

Keep out of reach of children. If product is swallowed, get medical help or contact a Poison Control Center right away.

OTHER SAFETY INFORMATION

Skin Cancer/Skin Aging Alert: Spending time in the sun increases you risk of skin cancer and early skin aging. this product has been shown only to prevent sunburn, not skin cancer or early aging.

Directions

- spray liberally and spread evenly by hand 15 minutes before sun exposure
- reapply:
  - after 80 minutes of swimming or sweating
  - immediately after towel drying
  - at least every 2 hours
- Children under 6 months: Ask a doctor
- hold container 4 to 6 inches from the skin to apply
- do not spray directly into face. Spray on hands then apply to face
- do not apply in windy conditions
- use in well-ventilated area

Inactive Ingredients

Acrylates/C10-30 Alkyl Acrylate Crosspolymer, Acrylates/C12-22 Alkyl Methacrylate Copolymer, Aloe Barbadensis Leaf Juice, Butylphthalimide, C12-15 Alkyl Benzoate, Camellia Sinensis (Green Tea) Leaf Extract, Caramel, Dimethicone, Disodium EDTA, Ethylhexylglycerin, Fragrance, Isopropylphthalimide, Oleth-10, Phenoxyethanol, Propylene Glycol, Retinyl Palmitate, Sodium Hydroxide, Sorbitan Oleate, Theobroma Cacao (Cocoa) Seed Butter, Tocopheryl Acetate, Trimethylsiloxysilicate, Ubiquinone, Water

Other information

- protect this product from excesive heat and direct sun
- May stain some fabrics

Questions or Comments?

Call toll free 1 800 840-5225